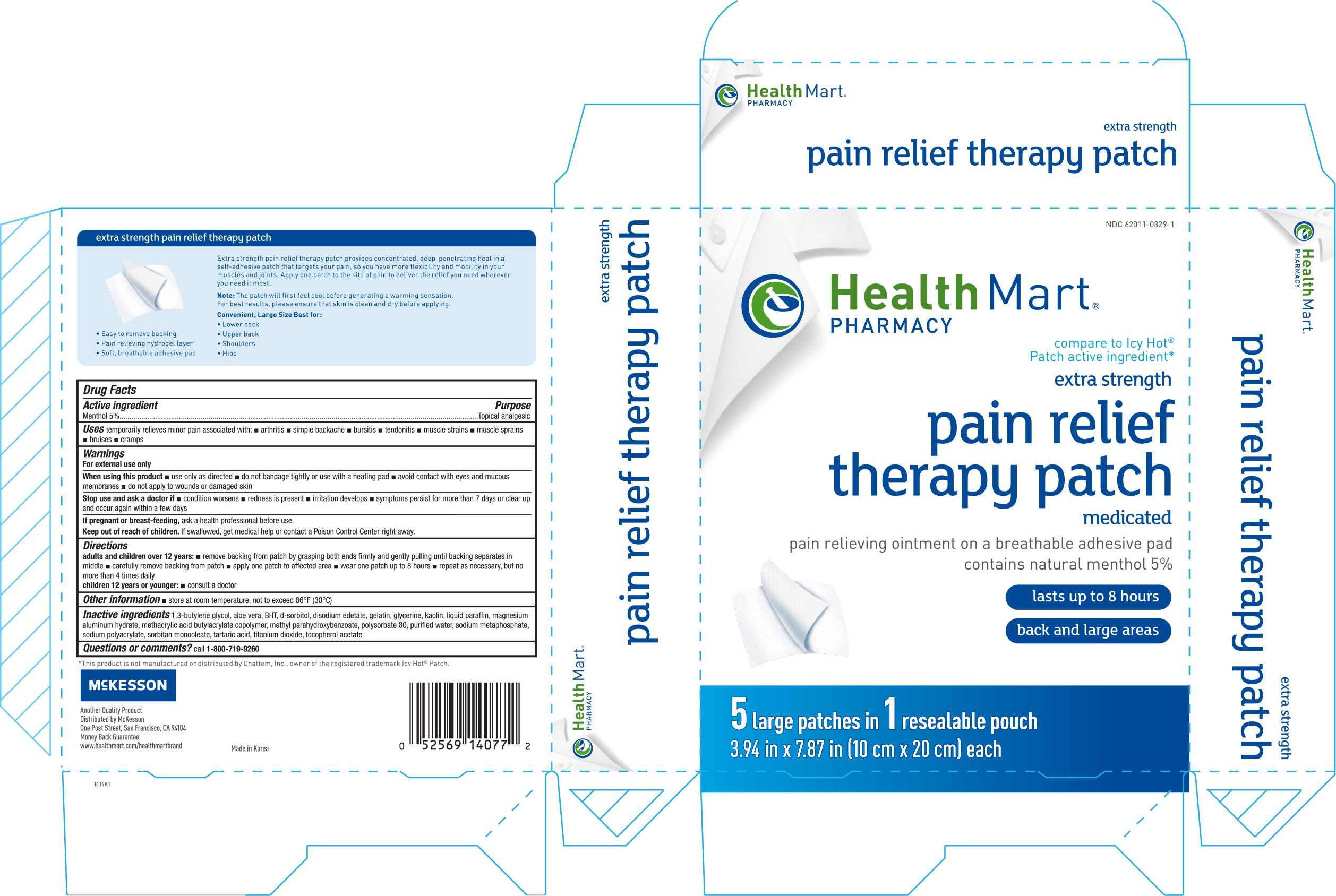 DRUG LABEL: Health Mart Extra Strength Pain Relief
NDC: 62011-0329 | Form: PATCH
Manufacturer: McKesson
Category: otc | Type: HUMAN OTC DRUG LABEL
Date: 20171212

ACTIVE INGREDIENTS: MENTHOL 428.5 mg/1 1
INACTIVE INGREDIENTS: BUTYLENE GLYCOL; ALOE VERA LEAF; BUTYLATED HYDROXYTOLUENE; SORBITOL; EDETATE DISODIUM; GELATIN; GLYCERIN; KAOLIN; PARAFFIN; MAGALDRATE; METHYLPARABEN; POLYSORBATE 80; WATER; SODIUM METAPHOSPHATE; SODIUM POLYACRYLATE (8000 MW); TARTARIC ACID; TITANIUM DIOXIDE; .ALPHA.-TOCOPHEROL ACETATE

Health Mart Pain Relief Therapy Patch 5ct, Large NBE Icy Hot

Active ingredient Purpose

Menthol 5%...................................................Topical analgesic

PURPOSE

Uses temporarily relieves pain associated with:

- arthritis
- simple backache
- bursitis
- tendonitis
- muscle strains
- muscle sprains
- bruises
- cramps

Warnings

For external use only

When using this product

- use only as directed
- do not bandage tightly or use with a heating pad
- avoid contact with eyes and mucous membranes
- do not apply to wounds or damaged skin

Stop use and ask a doctor if

- condition worsens
- redness is present
- irritation develops
- symptoms persist for more than 7 days or clear up and occur again within a few days

PREGNANCY OR BREAST FEEDING

If pregnant or breast-feeding, ask a health professional before use.

Keep out of reach of children. If swallowed, get medical help or contact a Poision Control Center right away.

Directions

adults and children over 12 years:

- remove backing from patch by grasping both ends firmly and gently pulling until backing separates in middle
- carefully remove backing from patch
- apply one patch to affected area
- wear one patch up to 8 hours
- repeat as necassary, but no more than 4 times daily

children 12 years or younger:

- consult a doctor

Other information

- store at room temperature, not to exceed 86°F (30°C)

Inactive ingredients

1,3 butylene glcol, aloe vera, BHT, d-sorbitol, disodium edetate, gelatin, glycerin, kaolin, liquid paraffin, magnesium aluminum hydrate, methacrylic acid butylacrylate copolymer, methyl parahydroxybenzoate, polysorbate 80, purified water, sodium metaphosphate, sodium polyacrylate, sorbitan monooleate, tartaric acid, titanium dioxide, tocopherol acetate

DOSAGE AND ADMINISTRATION

Distributed by:

McKesson

One Post Street

San Franciso, CA 94104

Made in Korea